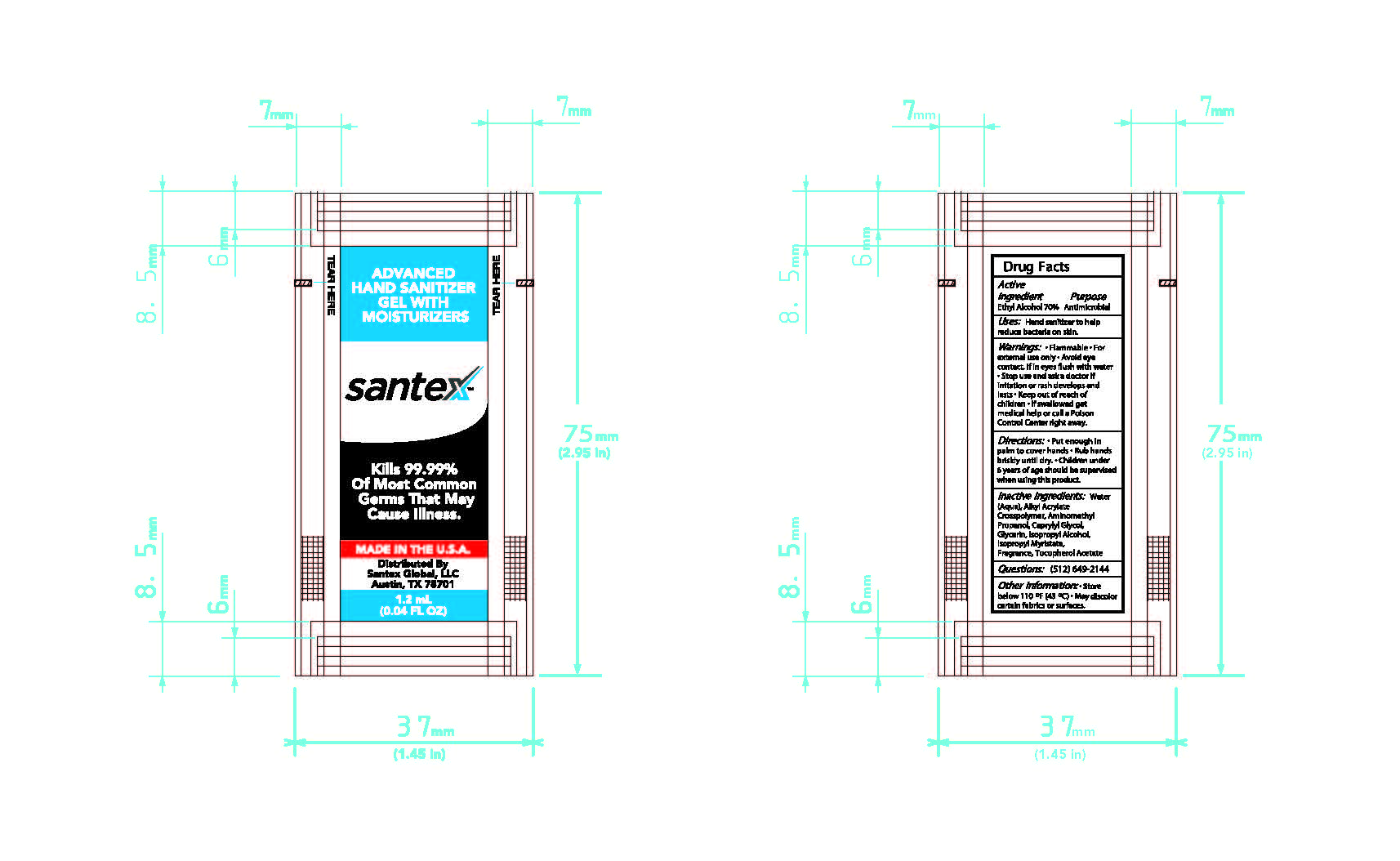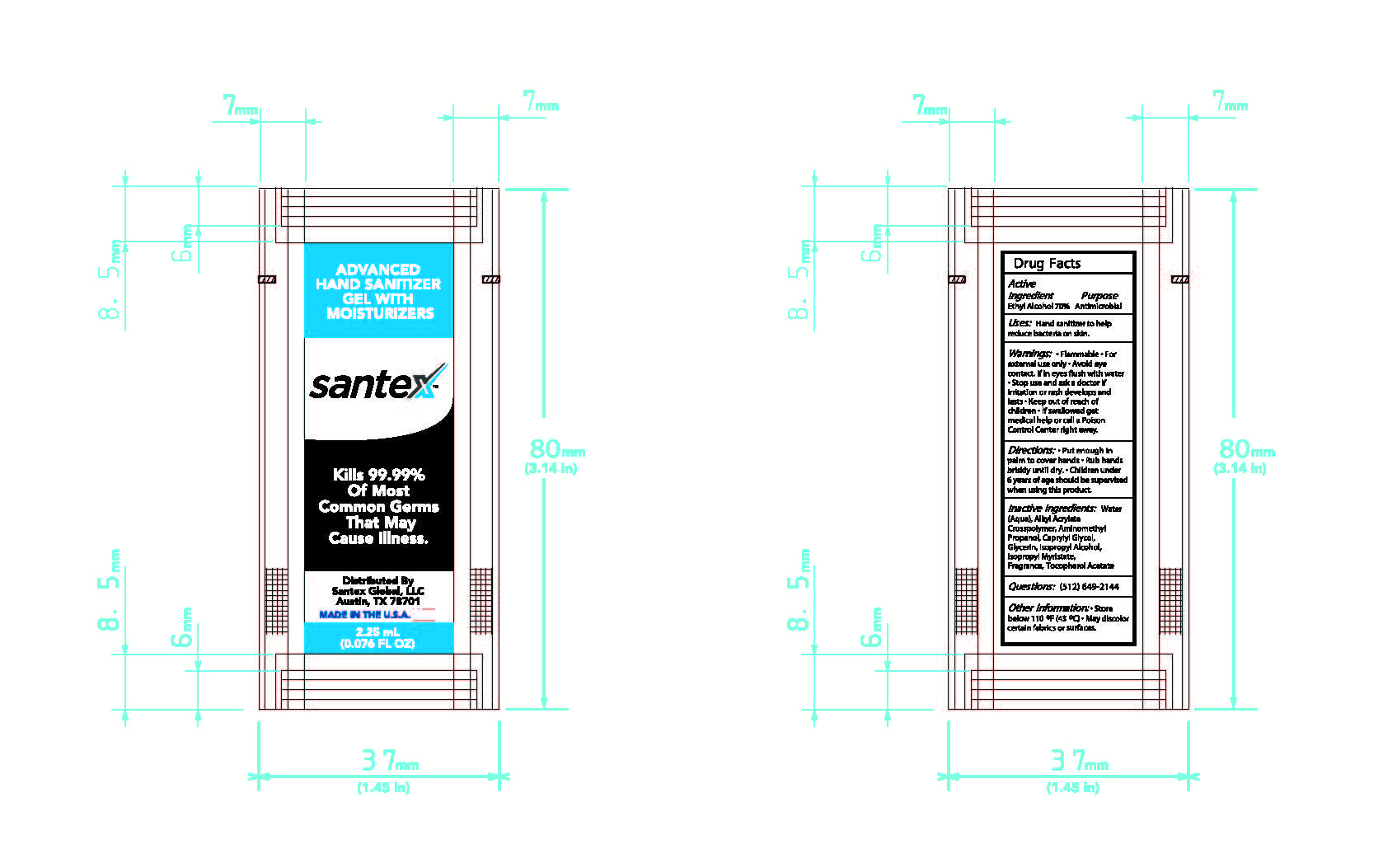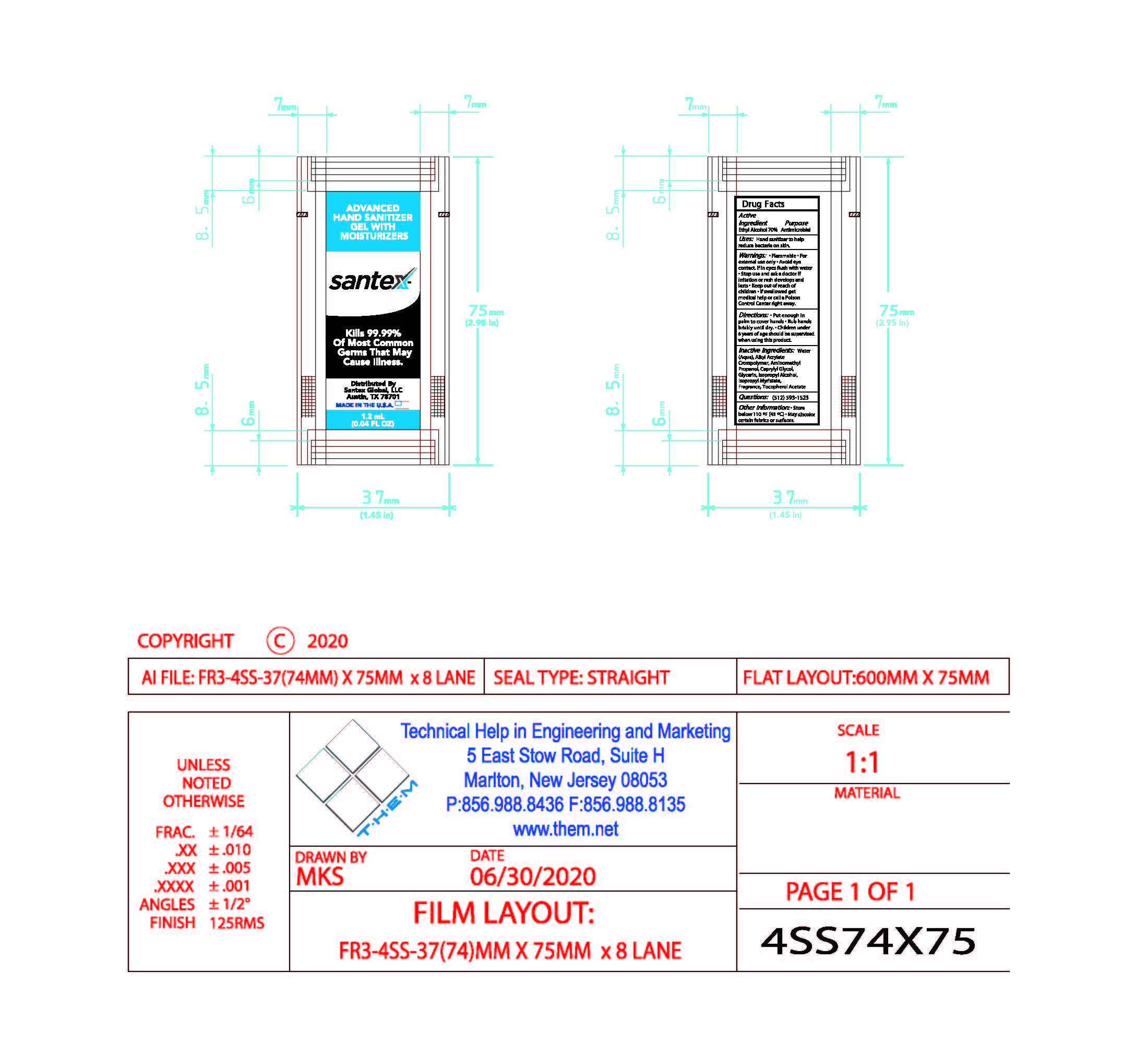 DRUG LABEL: Santex Gel Hand Sanitizer
NDC: 78618-001 | Form: GEL
Manufacturer: Santex Global, LLC
Category: otc | Type: HUMAN OTC DRUG LABEL
Date: 20200709

ACTIVE INGREDIENTS: ALCOHOL 70 g/100 g
INACTIVE INGREDIENTS: .ALPHA.-TOCOPHEROL ACETATE, D-; CARBOMER INTERPOLYMER TYPE A (55000 CPS); GLYCERIN; WATER; AMINOMETHYL PROPANEDIOL; ISOPROPYL ALCOHOL; FRAGRANCE LAVENDER & CHIA F-153480; ISOPROPYL MYRISTATE; CAPRYLYL GLYCOL

Santex Hand Sanitizer

Active Ingredients

Active Ingredient Purpose

Ethyl Alcohol 70% Antimicrobial

Santex Hand Sanitizer 1.2 mL Package NDC 78618-001-01

NDC 78618-001-01 1.2 mL Package

Purpose

Hand Sanitizer to Help Reduce Bacteria on Skin

Directions for Use

Put enough on palms to cover hands. Rub hands briskly until dry. Children under 6 should be supervised when using this product.

Warnings

- Flammable
- For external use only
- Avoid eye contact, if in eyes flush with water

Stop Use

Stop use and ask a doctor if irritation or rash develops and lasts.

Keep Out of Reach of Children

If swallowed get medical help or call a poison control center right away

Inactive Ingredients

Inactive Ingredients: Water (Aqua), Alkylacrylate Cross Polymer, Aminomethyl Propanol, Caprylyl Glycol, Glycerin, Isopropyl Alcohol, Isopropyl Myristate, Fragrance, Tocopherol Acetate

Directions and Usage

Put enough in palm to cover hands. Rub hands briskly until dry.

Indications and Usage

Hand Sanitizer to help reducer bacteria on skin.

NDC 78618-001-02 2.25 mL Package

NDC 78618-001-02

2.25 mL Size

Image: 2.25 mL Art.jpg

Package Pricipal Display Panel 1.2 mL Package

NDC 78618-001-01

1.2 mL Package

Image 1-2 mK Art.jpg

Principal Display Panel 2.25 mL Package

NDC 78618-001-02

2.25 mL Package

Image 2-25 mL Art.jpg